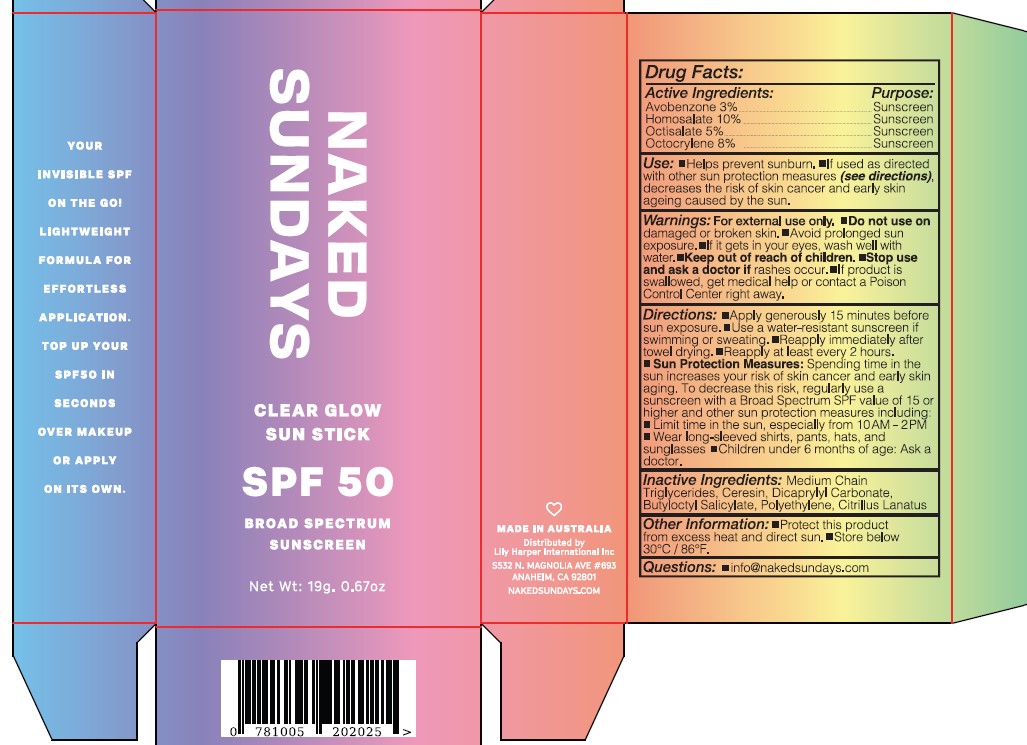 DRUG LABEL: CLEAR GLOW BROAD SPECTRUM SUNCREEN

NDC: 81104-984 | Form: CREAM
Manufacturer: NAKED SUNDAYS PTY LTD
Category: otc | Type: HUMAN OTC DRUG LABEL
Date: 20250401

ACTIVE INGREDIENTS: AVOBENZONE 3 g/100 g; HOMOSALATE 10 g/100 g; OCTISALATE 5 g/100 g; OCTOCRYLENE 8 g/100 g
INACTIVE INGREDIENTS: CERESIN; DICAPRYLYL CARBONATE; TOMATO JUICE; HIGH DENSITY POLYETHYLENE; BUTYLOCTYL SALICYLATE

NAKED SUNDAYS CLEAR GLOW SUN STICK SPF 50 BROAD SPECTRUM SUNCREEN 19G

ACTIVE INGREDIENTS

Avobenzone 3%

Homosalate 10%

Octilsalate 5%

Octocrylene 8%

Purpose

Sunscreen

USES

Helps prevent sunburn. If used as directed
with other sun protection measures (see directions),
decreases the risk of skin cancer and early skin
ageing caused by the sun.

WARNINGS

Warnings: For external use only. Do not use on
damaged or broken skin. Avoid prolonged sun
exposure. If it gets in your eyes, wash well with
water. Keep out of reach of children. Stop use
and ask a doctor if rashes occur. If product is
swallowed, get medical help or contact a Poison
Control Center right away.

Keep out of reach of children. If product is swallowed, get medical help or contact a Poison Control Center right away.

DIRECTIONS

- SPRAY 7 TIMES WITH MOUTH AND LIPS CLOSED 8-10" AWAY FROM FACE 15 MINUTES BEFORE SUN EXPOSURE.
- Reapply after 80 minutes of swimming or sweating.
- Reapply immediately after towel drying.
- Reapply at least every 2 hours.
- Children under 3 years of age: Ask a doctor.

SUN PROTECTION MEASURES:

Spending time in the sun increases your risk of skin cancer and early skin aging. To decrease this risk, regularly use a sunscreen with a Broad Spectrum SPF value of 15 or higher and other sun protection measures including:

- Limit time in the sun, especially from 10.00AM - 2.00PM
- Wear long-sleeved shirts, pants, hats, and sunglasses

INACTIVE INGREDIENTS

Inactive Ingredients: Medium Chain
Triglycerides, Ceresin, Dicaprylyl Carbonate,
Butyloctyl Salicylate, Polyethylene, Citrillus Lanatus

OTHER INFORMATION

Other Information: Protect this product
from excess heat and direct sun. Store below
30°C / 86°F.

RECENT MAJOR CHANGES

Helps prevent sunburn. If used as directed
with other sun protection measures (see directions),
decreases the risk of skin cancer and early skin
ageing caused by the sun.

USER SAFETY WARNINGS

Directions: Apply generously 15 minutes before
sun exposure. Use a water-resistant sunscreen if
swimming or sweating. Reapply immediately after
towel drying. Reapply at least every 2 hours.
Sun Protection Measures: Spending time in the
sun increases your risk of skin cancer and early skin
aging. To decrease this risk, regularly use a
sunscreen with a Broad Spectrum SPF value of 15 or
higher and other sun protection measures including:
Limit time in the sun, especially from 10AM - 2PM
Wear long-sleeved shirts, pants, hats, and
sunglasses Children under 6 months of age: Ask a
doctor.